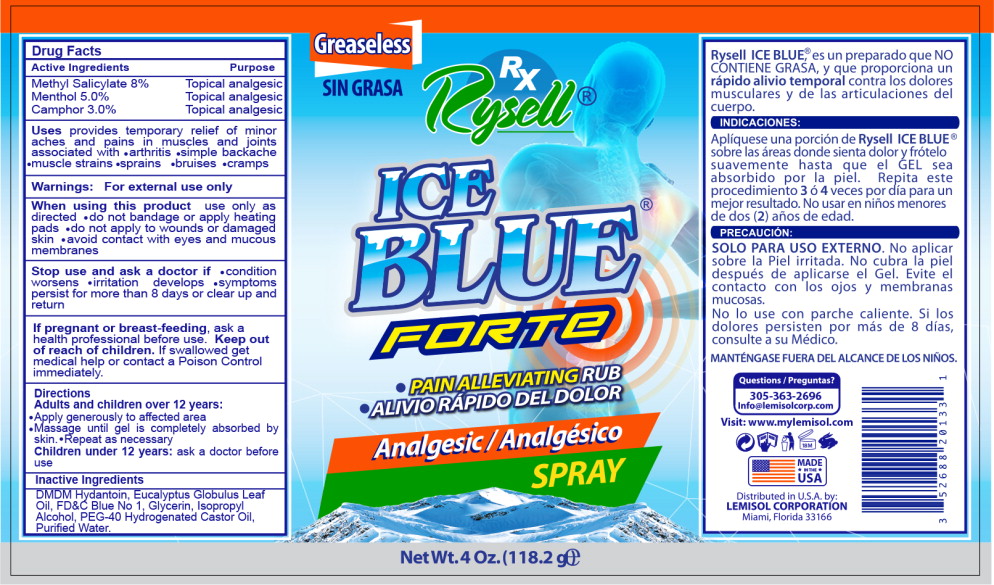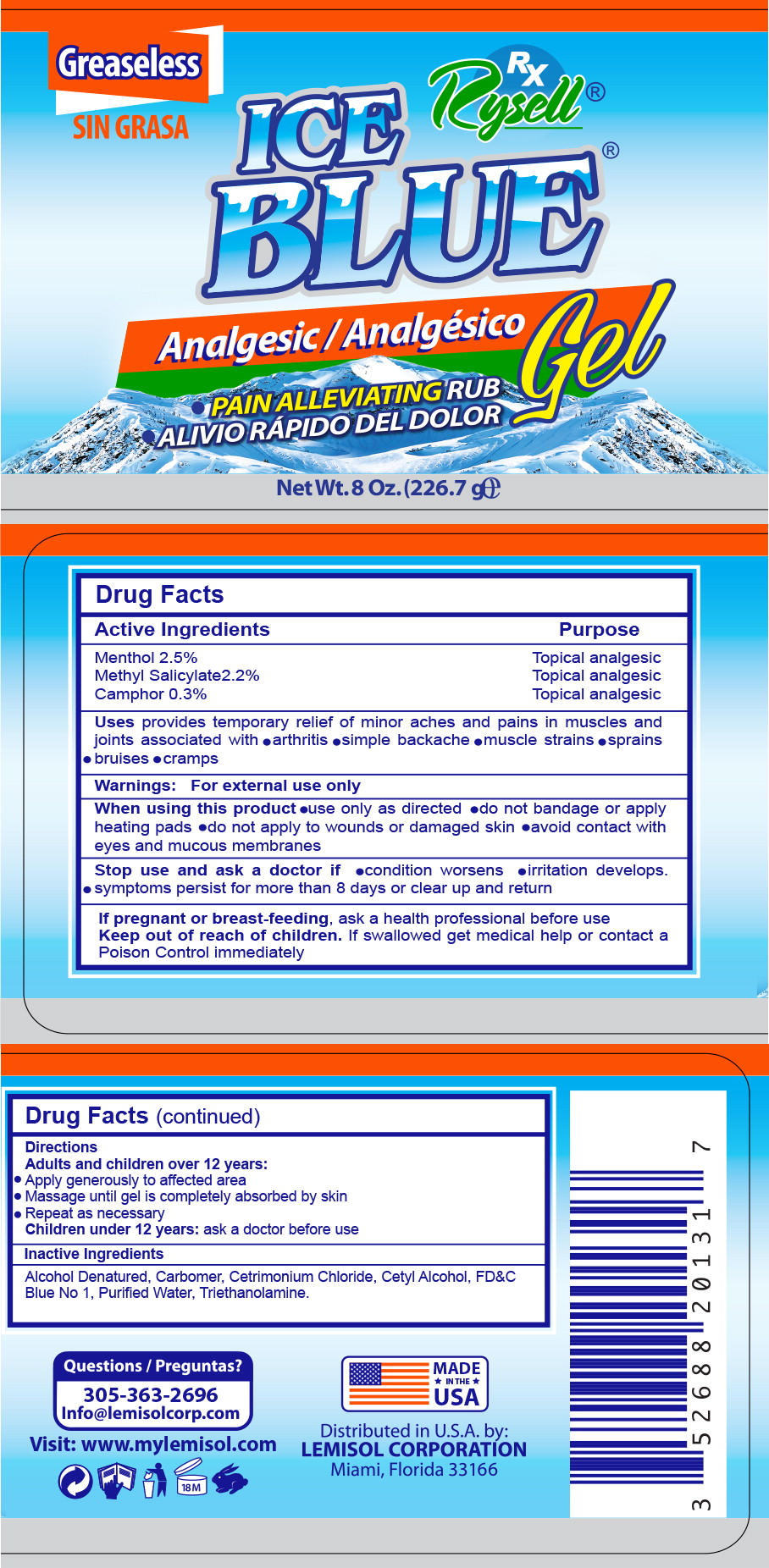 DRUG LABEL: Ice Blue Pain Alleviating Rub
NDC: 82988-101 | Form: GEL
Manufacturer: Lemisol Corporation
Category: otc | Type: HUMAN OTC DRUG LABEL
Date: 20220831

ACTIVE INGREDIENTS: MENTHOL, UNSPECIFIED FORM 0.025 g/1 g; METHYL SALICYLATE 0.022 g/1 g; CAMPHOR (NATURAL) 0.003 g/1 g
INACTIVE INGREDIENTS: ALCOHOL; CARBOMER HOMOPOLYMER, UNSPECIFIED TYPE; CETRIMONIUM CHLORIDE; CETYL ALCOHOL; FD&C BLUE NO. 1; WATER; TROLAMINE

Drug Facts

Active Ingredients

Methyl Salicylate8%

Menthol 5.0%

Camphor 3.0%

Purpose

Topical analgesic

Topical analgesic

Topical analgesic

INDICATIONS AND USAGE

Uses provides temporary relief of minor aches and pains in muscles and joints associated with

- arthritis
- simple backache
- muscle strains
- sprains
- bruises
- cramps

Warnings:

For external use only

When using this product use only as directed

- do not bandage or apply heating pads
- do not apply to wounds or damaged skin
- avoid contact with eyes and mucous membranes

Stop use and ask a doctor if

- condition worsens
- irritation develops
- symptoms persist for more than 8 days or clear up and return

PREGNANCY OR BREAST FEEDING

If pregnant or breast-feeding, ask a health professional before use.

Keep out of reach of children. If swallowed get medical help or contact a Poison Control immediately.

Directions

Adults and children over 12 years:

Apply generously to affected area

Massage until gel is completely absorbed by skin. Repeat as necessary

Inactive Ingredients

DMDM Hydantoin, Eucalyptus Globulus Leaf Oil, FD&C Blue No 1, Glycerin, Isopropyl Alcohol, PEG-40 Hydrogenated Castor Oil, Purified Water.

Principal Display Panel – 8 oz Spray Label

Greaseless

SIN GRASA

Rx
Rysell®

ICE
BLUE®
FORTE

- PAIN ALLEVIATING RUB
- ALIVIO RÁPIDO DEL DOLOR

Analgesic/ Analgésico

SPRAY

Net Wt. 4 Oz. (118.2 g)e

Principal Display Panel – 8 oz Gel Label

Greaseless

SIN GRASA

Rx
Rysell®

ICE
BLUE®

Analgesic/ Analgésico

Gel

- PAIN ALLEVIATING RUB
- ALIVIO RÁPIDO DEL DOLOR

Net Wt. 8 Oz. (226.7 g)e